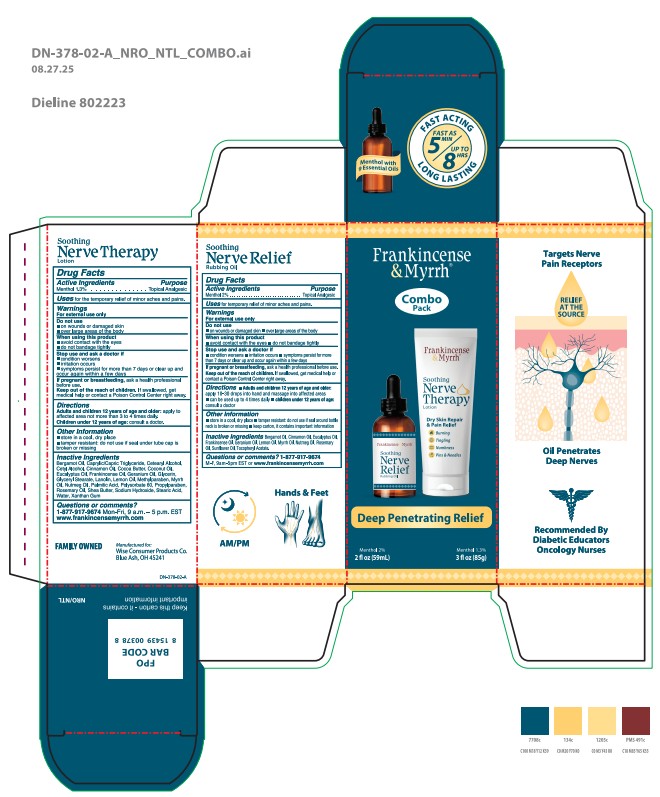 DRUG LABEL: Frankincense and Myrrh Nerve Combo Pack
NDC: 42346-378 | Form: KIT | Route: TOPICAL
Manufacturer: Wise Consumer Products
Category: otc | Type: HUMAN OTC DRUG LABEL
Date: 20251229

ACTIVE INGREDIENTS: MENTHOL 20 mg/1 mL; MENTHOL 1.3 g/100 g
INACTIVE INGREDIENTS: CINNAMON OIL; EUCALYPTUS OIL; GERANIUM OIL, ALGERIAN TYPE; NUTMEG OIL; LEMON OIL; BERGAMOT OIL; FRANKINCENSE OIL; .ALPHA.-TOCOPHEROL ACETATE; ROSEMARY OIL; MYRRH OIL; SUNFLOWER OIL; XANTHAN GUM; EUCALYPTUS OIL; WATER; MYRRH OIL; COCOA BUTTER; LANOLIN; CETEARYL ALCOHOL; METHYLPARABEN; SHEA BUTTER; LEMON OIL; STEARIC ACID; GERANIUM OIL, ALGERIAN TYPE; CAPRYLIC/CAPRIC TRIGLYCERIDE; COCONUT OIL; GLYCERYL STEARATE; BERGAMOT OIL; GLYCERIN; POLYSORBATE 60; CETYL ALCOHOL; ROSEMARY OIL; SODIUM HYDROXIDE; FRANKINCENSE OIL; NUTMEG OIL; PROPYLPARABEN; CINNAMON OIL; PALMITIC ACID

Frankincense and Myrrh Nerve Combo Pack

42346-550-86

Active ingredient

Menthol 1.3%

Purpose

Menthol 1.3%......................Topical Analgesic

Uses

For the temporary relief of minor aches and pains.

Warnings

For external use only

When using this product

- avoid contact with the eyes
- do not bandage tightly

Do not use

- on wounds or damaged skin
- over large areas of the body

Stop use and ask a doctor if

- condition worsens
- irritation occurs
- symptoms persist for more than 7 days or clear up and occur again within a few days

PREGNANCY OR BREAST FEEDING

If pregnant or breastfeeding, ask a health professional before use.

KEEP OUT OF REACH OF CHILDREN

Keep out of the reach of children. If swallowed, get medical help or contact a Poison Control Center right away.

Directions

Adults and children 12 years of age and older: apply to affected area not more than 3 to 4 times daily.

Children under 12 years of age: consult a doctor.

Other information

- store in a cool, dry place
- tamper resistant: do not use if seal undertube cap is broken or missing

Inactive ingredients

Bergamot Oil, Caprylic/Capric Triglyceride, Cetearyl Alcohol, Cetyl Alcohol, Cinnamon Oil, Cocoa Butter, Coconut Oil, Eucalyptus Oil, Frankincense Oil, Geranium Oil, Glycerin, Glyceryl Stearate, Lanolin, Lemon Oil, Methylparaben, Myrrh Oil, Nutmeg Oil, Palmitic Acid, Polysorbate 60, Propylparaben, Rosemary Oil, Shea Butter, Sodium Hydroxide, Stearic Acid, Water, Xanthan Gum

Questions or comments?

1-877-917-9674 Monday – Friday, 9 a.m.–5 p.m. ESTor visit www.frankincensemyrrh.com

42346-360-59

Active ingredient

Menthol 2%

Purpose

Menthol 2%......................Topical Analgesic

Uses

For temporary relief of minor aches and pains

Warnings

For external use only

Do not use

- on wounds or damaged skin
- over large areas of the body

When using this product

- avoid contact with the eyes
- do not bandage tightly

Stop use and ask a doctor if

- condition worsens
- irritation occurs
- symptoms persist for more than 7 days or clear up and occur again within a few days

PREGNANCY OR BREAST FEEDING

If pregnant or breastfeeding, ask a health professional before use.

KEEP OUT OF REACH OF CHILDREN

Keep out of reacho f children. If swallowed, get medical help or contact a Poison Control Center right away.

Directions

- Adults and children 12 years of age and older:
- apply 10-30 drops into hand and massage into affected areas
- can be used up to 4 times daily
- children under 12 years of age: consult a doctor

Other information

- store in a cool, dry place
- tamper resistant: do not use if seal around bottle neck is broken or missing
- keep carton, it contains important information

Inactive ingredients

Bergamot Oil, Cinnamon Oil, Eucalyptus Oil, Frankincense Oil, Geranium Oil, Lemon Oil, Myrrh Oil, Nutmeg Oil, Rosemary Oil, Sunflower Oil, Tocopheryl Acetate

Questions or comments?

1-877-917-9674

M-F, 9am-5pm EST or www.frankincensemyrrh.com

PACKAGE LABEL

Frankincense & Myrrh

Combo Pack

Deep Penetrating Relief

Menthol 2%

2 fl oz (59mL)

Menthol 1.3%

3 fl oz (85g)